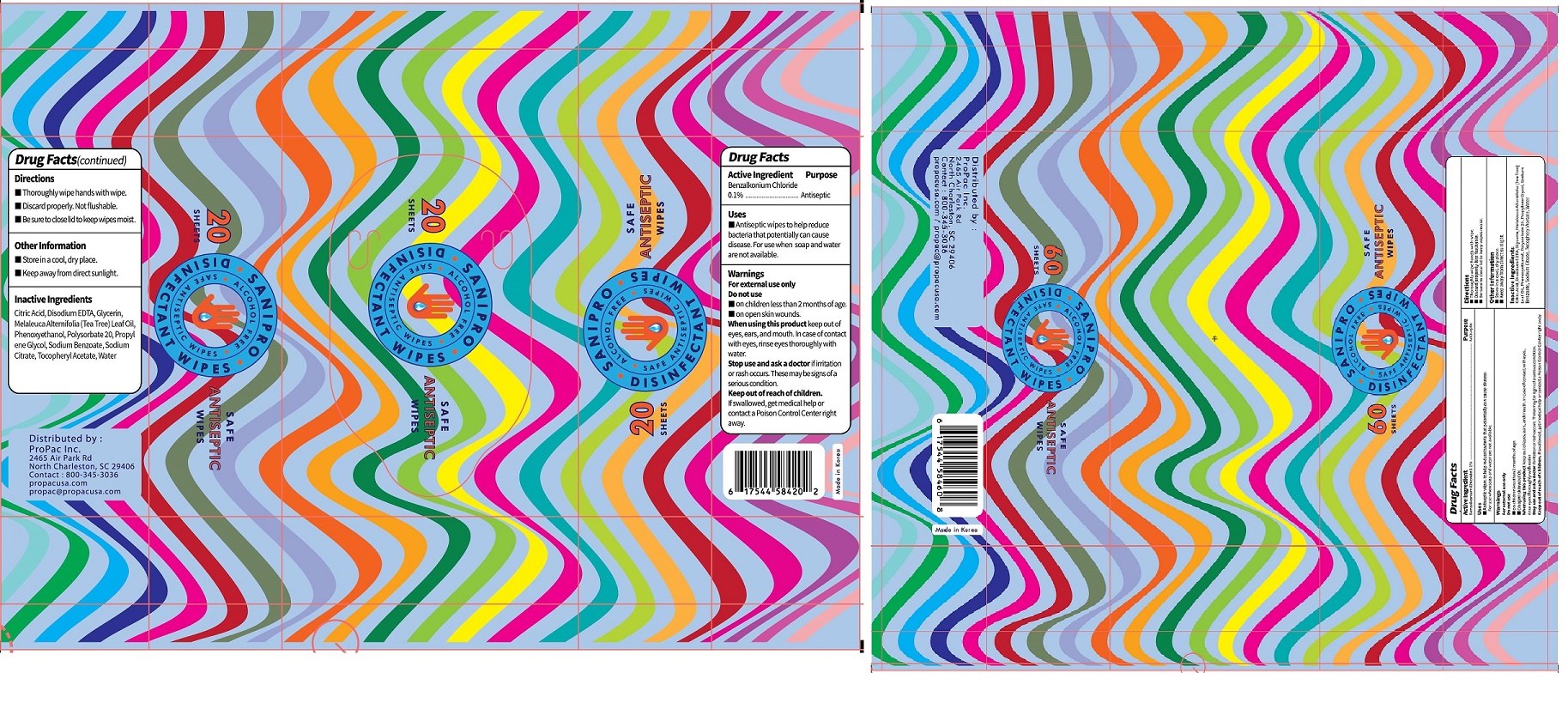 DRUG LABEL: SANIPRO DISINFECTANT WIPES
NDC: 75356-0005 | Form: CLOTH
Manufacturer: AJ Co., Ltd.
Category: otc | Type: HUMAN OTC DRUG LABEL
Date: 20201007

ACTIVE INGREDIENTS: BENZALKONIUM CHLORIDE 0.1 g/100 g
INACTIVE INGREDIENTS: WATER

ACTIVE INGREDIENT

Benzalkonium Chloride

INACTIVE INGREDIENT

Propylene Glycol
Phenoxyethanol
Glycerin
Sodium Benzoate
Sodium Citrate
Disodium EDTA
Polysorbate 20
Citric Acid
Melaleuca Alternifolia (Tea Tree) Leaf Oil
Tocopheryl Acetate

PURPOSE

Antibacterial Wipes to help reduce bacteria that potentially can cause disease. For use when soap and water are not available.

keep out of reach of the children

INDICATIONS AND USAGE

Thoroughly wipe hands with wipe.

Discard properly. Not flushable.

Be sure to close lid to keep wipes moist.

WARNINGS

For external use only. Flammable. Keep away from heat or flame.

Do not use

- in children less than 2 months of age
- on open skin wounds

When using this product keep out of eyes, ears, and mouth. In case of contact with eyes, rinse thoroughly with water.

Stop use and ask a doctor if irritation or rash occurs. These may be signs of a serious condition.

Keep out of reach of children. If swallowed, get medical help or contact a Poison Control Center right away.

DOSAGE AND ADMINISTRATION

for external use only